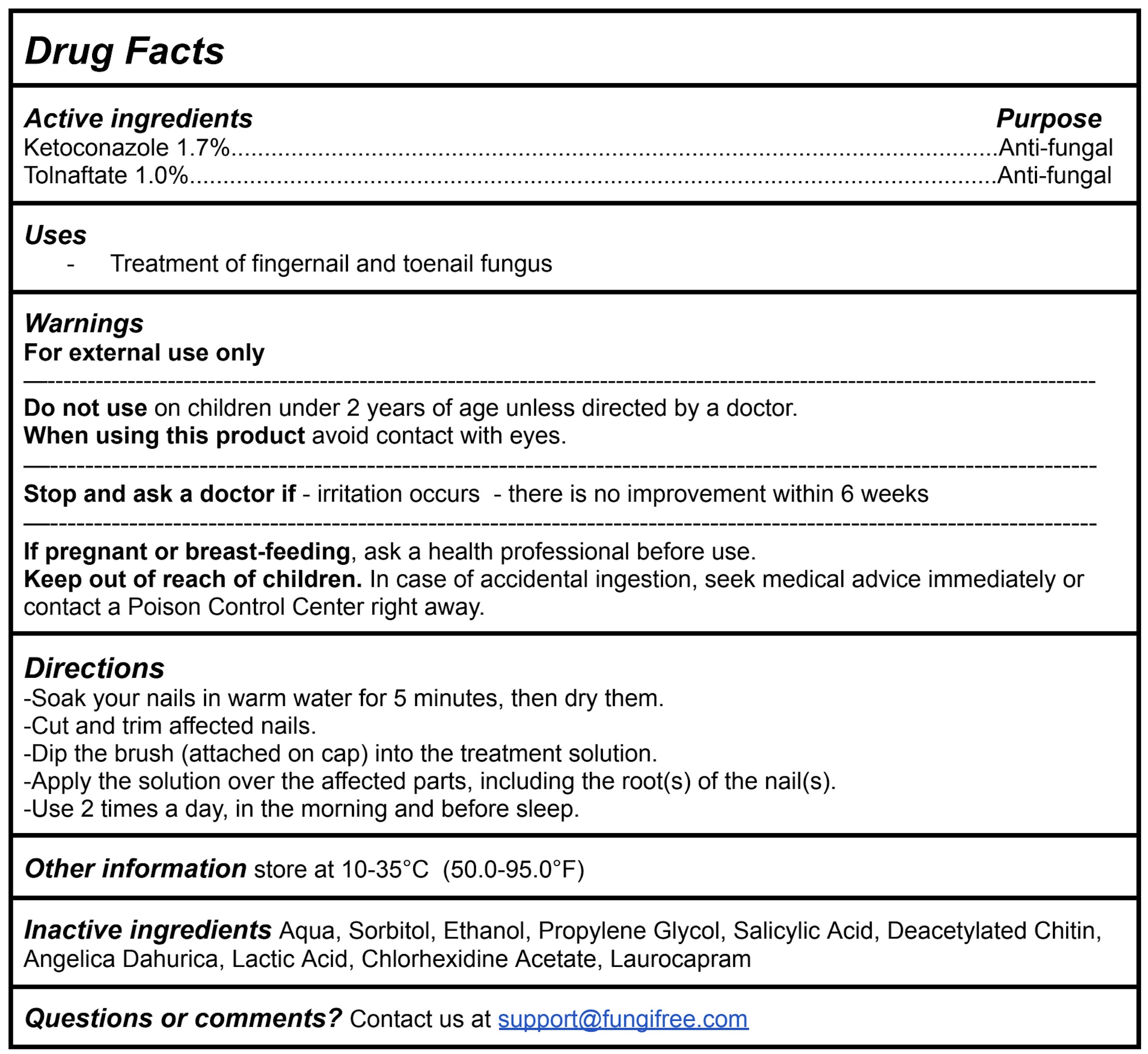 DRUG LABEL: FungiFree Nail Fungus Treatment
NDC: 83364-005 | Form: SOLUTION
Manufacturer: YITONGBADA (SHENZHEN) INTERNATIONAL TRADE CO., LTD
Category: otc | Type: HUMAN OTC DRUG LABEL
Date: 20240514

ACTIVE INGREDIENTS: KETOCONAZOLE 1.7 g/100 g; TOLNAFTATE 1 g/100 g
INACTIVE INGREDIENTS: LACTIC ACID; CHLORHEXIDINE ACETATE; LAUROCAPRAM; SORBITOL; ALCOHOL; ANGELICA DAHURICA VAR. FORMOSANA WHOLE; WATER; PROPYLENE GLYCOL; POLIGLUSAM; SALICYLIC ACID

PACKAGE LABEL

Active ingredients Purpose

Ketoconazole 1.7%...................................................................................................................Anti-fungal

Tolnaftate 1.0%.........................................................................................................................Anti-fungal

PURPOSE

Treatment of fingernail and toenail fungus

Uses

DOSAGE AND ADMINISTRATION

For external use only

Do not use on children under 2 years of age unless directed by a doctor.

When using this product avoid contact with eyes.

ASK DOCTOR

Stop and ask a doctor if - irritation occurs - there is no improvement within 6 weeks

PREGNANCY OR BREAST FEEDING

If pregnant or breast-feeding, ask a health professional before use.

Keep out of reach of children. In case of accidental ingestion, seek medical advice immediately or contact a Poison Control Center right away.

Warnings

Directions

-Soak your nails in warm water for 5 minutes, then dry them.

-Cut and trim affected nails.

-Dip the brush (attached on cap) into the treatment solution.

-Apply the solution over the affected parts, including the root(s) of the nail(s).

-Use 2 times a day, in the morning and before sleep.

INACTIVE INGREDIENT

Inactive ingredients Aqua, Sorbitol, Ethanol, Propylene Glycol, Salicylic Acid, Deacetylated Chitin, Angelica Dahurica, Lactic Acid, Chlorhexidine Acetate, Laurocapram

Other information store at 10-35°C (50.0-95.0°F)